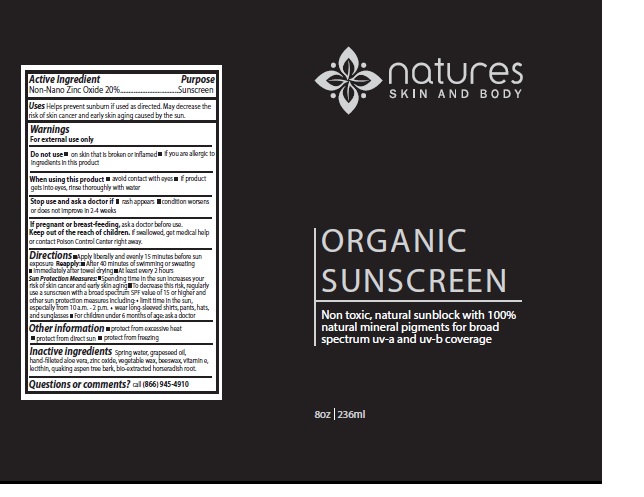 DRUG LABEL: Organic Sunscreen
NDC: 71371-001 | Form: CREAM
Manufacturer: NATURE'S NATURAL PRODUCTS, INC
Category: otc | Type: HUMAN OTC DRUG LABEL
Date: 20170329

ACTIVE INGREDIENTS: ZINC OXIDE 20 g/100 mL
INACTIVE INGREDIENTS: WATER; GRAPE SEED OIL; ALOE VERA LEAF; POPULUS ALBA BARK; YELLOW WAX; TOCOPHEROL; LECITHIN, SOYBEAN; HORSERADISH

Organic Sunscreen

Actives

Non-Nano Zinc Oxide 20 %

Inactives

Spring water, Grapeseed oil, Aloe vera, Vegtable wax,Beeswax, Vitamin E, Lecithin, aspen tree bark, fermented horseradish root

Purpose

Helps prevent sunburn if used as directed

Directions

Sun Protection Measures:Spending time in the sun increases your risk of skin cancer and early skin aging
To decrease this risk, regularly use a sunscreen with Broad Spectrum SPF value of 15 or higher and other sun protection measures including:

- Limit time in the sun, especially from 10am-2pm

- For children under 6 months of age: ask a doctor

- Wear long-sleeved shirts, pants, hats, and sunglasses

Warnings

For external use only.
Do not use on skin that is broken or inflamed if you are allergic to ingredients in this product
When using this product avoid contact with eyes if product gets into eyes, rinse thoroughly with water
Stop use and ask a doctor if rash appears, condition worsens or does not improve in 2-4 weeks
If pregnant or breast-feeding, ask a doctor before use.

Keep out of the reach of children. If swallowed, get medical help or contact Poison Control Center right away.